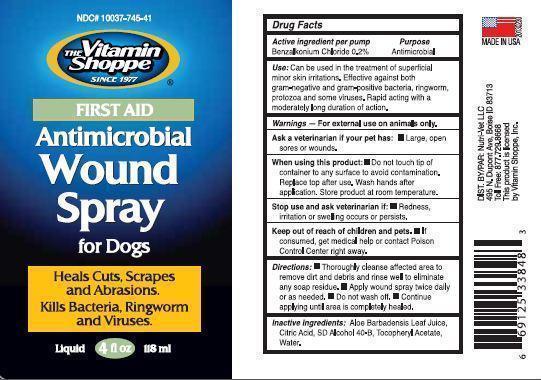 DRUG LABEL: Vitamin Shoppe
NDC: 10037-745 | Form: SPRAY
Manufacturer: Nutri-Vet LLC
Category: animal | Type: OTC ANIMAL DRUG LABEL
Date: 20130401

ACTIVE INGREDIENTS: BENZALKONIUM CHLORIDE 0.2 g/100 mL
INACTIVE INGREDIENTS: ALOE VERA LEAF; CITRIC ACID MONOHYDRATE; ALCOHOL; ALPHA-TOCOPHEROL, DL-; WATER

Drug Facts

Active ingredient per pump

Benzalkonium Chloride 0.2%

Purpose

Antimicrobial

INDICATIONS AND USAGE

Use: Can be used in the treatment of

superficial minor skin irritations. Effective against both gram-negative and

gram-positive bacteria, ringworm, protozoa

and some viruses.Rapid acting with a

moderately long duration of action.

Warnings

For external use on animals only

Ask a veterinarian if your pet has:

Large, open sores or wounds.

When using this product:

Do not touch tip of container to any surface to avoid contamination

Replace top after use. Wash hands after application. Store product at room temperature.

Stop use and ask veterinarian if:

Redness, irritation or swelling occurs or persists.

Keep out of reach of children and pets.

If consumed, get medical help or contact Poison Control Center right away.

Directions

Thoroughly cleanse affected area to remove dirt and debris and rinse well to eliminate any soap residue.

Apply WOUND SPRAY twice daily or as needed. Do not wash off.

Continue applying until area is completely healed.

INACTIVE INGREDIENT

Inactive Ingredients Aloe Barbadensis Leaf Juice, Citric Acid, SD Alcohol 40-B, Tocopheryl Acetate, Water.